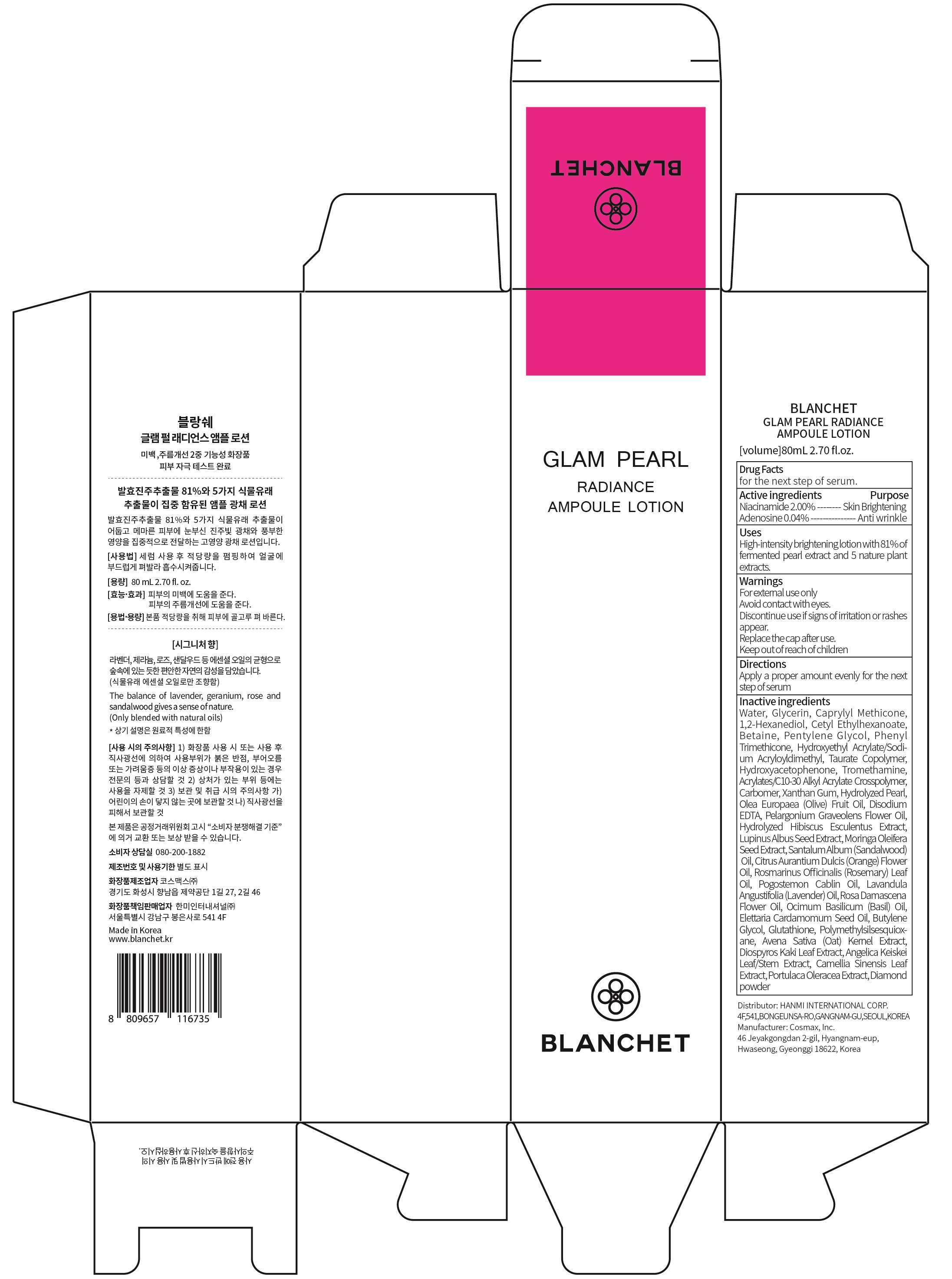 DRUG LABEL: BLANCHET GLAM PEARL RADIANCE AMPOULE
NDC: 79171-010 | Form: LOTION
Manufacturer: Hanmi International Corp.
Category: otc | Type: HUMAN OTC DRUG LABEL
Date: 20200806

ACTIVE INGREDIENTS: Niacinamide 1.60 g/80 mL; Adenosine 0.03 g/80 mL
INACTIVE INGREDIENTS: Water; Glycerin; CAPRYLYL TRISILOXANE

ACTIVE INGREDIENTS

Niacinamide 2.00%
Adenosine 0.04%

PURPOSE

Skin Brightening
Anti wrinkle

Uses

High-intnsity brightening lotion with 81% of fermented pearl extract and 5 nature plant extracts.

WARNINGS

For external use only
Avoid contact with eyes.
Discontinue use if signs of irritation or rashes appear.
Replace the cap after use.
Keep out of reach of children

KEEP OUT OF REACH OF CHILDREN

Directions

Apply a proper amount evenly for the next step of serum

INACTIVE INGREDIENT

Water, Glycerin, Caprylyl Methicone, 1,2-Hexanediol, Cetyl Ethylhexanoate, Betaine, Pentylene Glycol, Phenyl Trimethicone, Hydroxyethyl Acrylate/Sodium Acryloyldimethyl, Taurate Copolymer, Hydroxyacetophenone, Tromethamine, Acrylates/C10-30 Alkyl Acrylate Crosspolymer, Carbomer, Xanthan Gum, Hydrolyzed Pearl, Olea Europaea (Olive) Fruit Oil, Disodium EDTA, Pelargonium Graveolens Flower Oil, Hydrolyzed Hibiscus Esculentus Extract, Lupinus Albus Seed Extract, Moringa Oleifera Seed Extract, Santalum Album (Sandalwood) Oil, Citrus Aurantium Dulcis (Orange) Flower Oil, Rosmarinus Officinalis (Rosemary) Leaf Oil, Pogostemon Cablin Oil, Lavandula Angustifolia (Lavender) Oil, Rosa Damascena Flower Oil, Ocimum Basilicum (Basil) Oil, Elettaria Cardamomum Seed Oil, Butylene Glycol, Glutathione, Polymethylsilsesquioxane, Avena Sativa (Oat) Kernel Extract, Diospyros Kaki Leaf Extract, Angelica Keiskei Leaf/Stem Extract, Camellia Sinensis Leaf Extract, Portulaca Oleracea Extract, Diamond powder